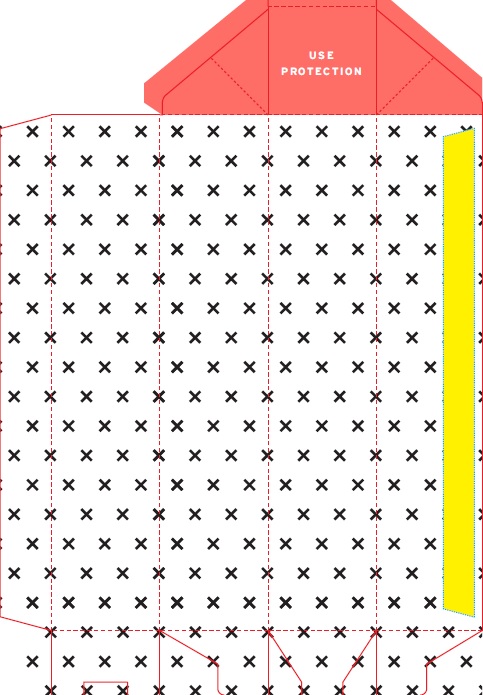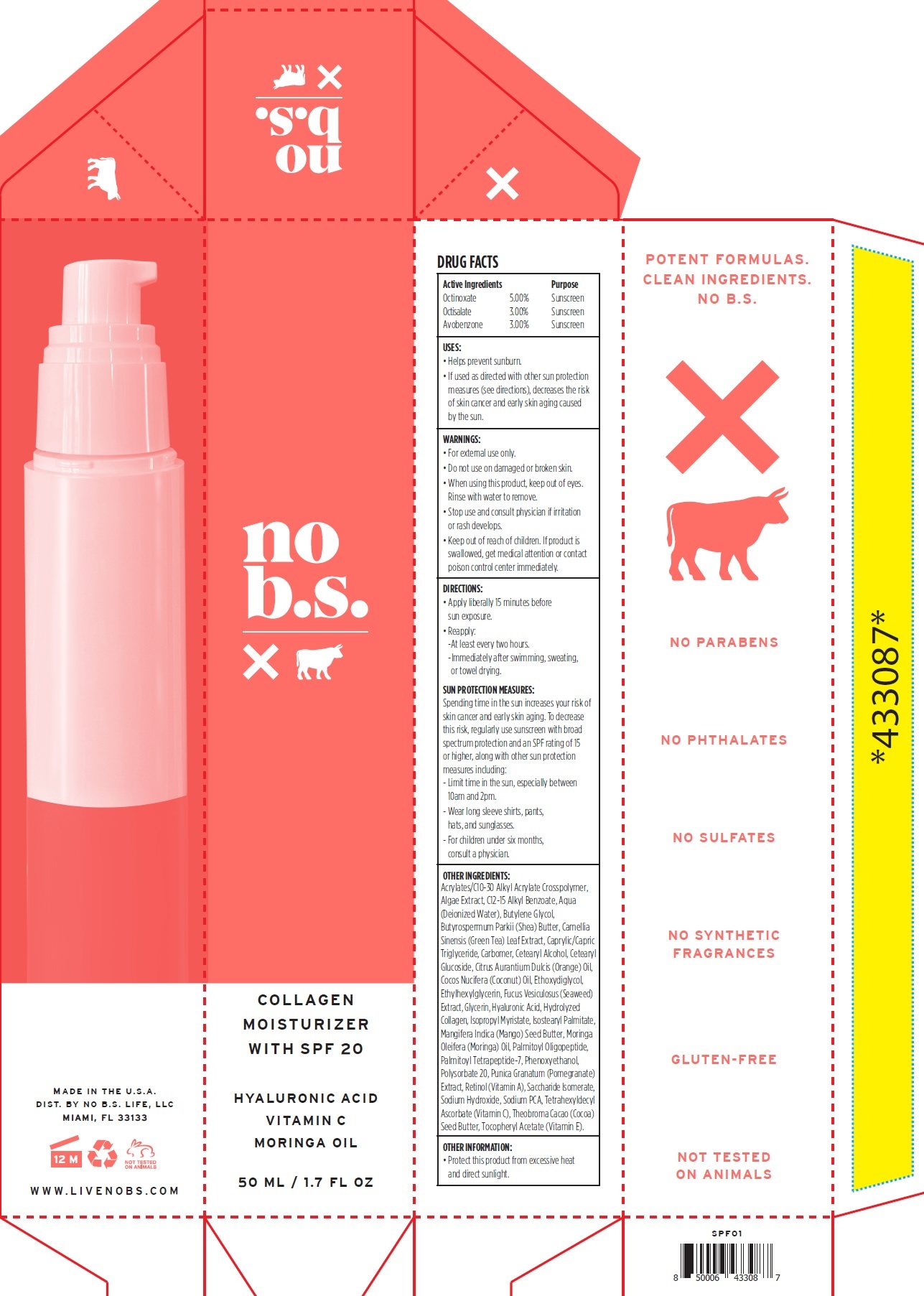 DRUG LABEL: NO BS Moisturizer SPF20
NDC: 71852-334 | Form: LOTION
Manufacturer: Product Management, LLC
Category: otc | Type: HUMAN OTC DRUG LABEL
Date: 20231105

ACTIVE INGREDIENTS: OCTINOXATE 50 mg/1 mL; OCTISALATE 30 mg/1 mL; AVOBENZONE 30 mg/1 mL
INACTIVE INGREDIENTS: ALKYL (C12-15) BENZOATE; WATER; BUTYLENE GLYCOL; SHEA BUTTER; GREEN TEA LEAF; MEDIUM-CHAIN TRIGLYCERIDES; CARBOXYPOLYMETHYLENE; CETOSTEARYL ALCOHOL; CETEARYL GLUCOSIDE; ORANGE OIL; COCONUT OIL; DIETHYLENE GLYCOL MONOETHYL ETHER; ETHYLHEXYLGLYCERIN; NORI; GLYCERIN; HYALURONIC ACID; ISOPROPYL MYRISTATE; ISOSTEARYL PALMITATE; MANGIFERA INDICA SEED BUTTER; PALMITOYL TRIPEPTIDE-1; PALMITOYL TETRAPEPTIDE-7; PHENOXYETHANOL; POLYSORBATE 20; POMEGRANATE; RETINOL; SACCHARIDE ISOMERATE; SODIUM HYDROXIDE; SODIUM PYRROLIDONE CARBOXYLATE; TETRAHEXYLDECYL ASCORBATE; COCOA BUTTER; .ALPHA.-TOCOPHEROL ACETATE

NO BS Moisturizer SPF20

Active Ingredients

Octinoxate 5.00%

Octisalate 3.00%

Avobenzone 3.00%

Purpose

Sunscreen

USES:

• Helps prevent sunburn. • If used as directed with other sun protection measures (see directions), decreases the risk of skin cancer and early skin aging caused by the sun.

WARNINGS:

• For external use only.

Do not use

- on damaged or broken skin.

When using this product

- keep out of eyes. Rinse with water to remove.

Stop use and consult physician

- if irritation or rash develops.

Keep out of reach of children.

If product is swallowed, get medical attention or contact poison control center immediately.

DIRECTIONS:

• Apply liberally 15 minutes before sun exposure. • Reapply: - At least every two hours. - Immediately after swimming, sweating, or towel drying.

Spending time in the sun increases your risk of skin cancer and early skin aging. To decrease this risk, regularly use sunscreen with broad spectrum protection and an SPF rating of 15 or higher, along with other sun protection measures including: - Limit time in the sun, especially between 10am and 2pm. - Wear long sleeve shirts, pants, hats, and sunglasses. - For children under six months, consult a physician. SUN PROTECTION MEASURES:

OTHER INGREDIENTS:

Acrylates/C10-30 Alkyl Acrylate Crosspolymer, Algae Extract, C12-15 Alkyl Benzoate, Aqua (Deionized Water), Butylene Glycol, Butyrospermum Parkii (Shea) Butter, Camellia Sinensis (Green Tea) Leaf Extract, Caprylic/Capric Triglyceride, Carbomer, Cetearyl Alcohol, Cetearyl Glucoside, Citrus Aurantium Dulcis (Orange) Oil, Cocos Nucifera (Coconut) Oil, Ethoxydiglycol, Ethylhexylglycerin, Fucus Vesiculosus (Seaweed) Extract, Glycerin, Hyaluronic Acid, Hydrolyzed Collagen, Isopropyl Myristate, Isostearyl Palmitate, Mangifera Indica (Mango) Seed Butter, Moringa Oleifera (Moringa) Oil, Palmitoyl Oligopeptide, Palmitoyl Tetrapeptide-7, Phenoxyethanol, Polysorbate 20, Punica Granatum (Pomegranate) Extract, Retinol (Vitamin A), Saccharide Isomerate, Sodium Hydroxide, Sodium PCA, Tetrahexyldecyl Ascorbate (Vitamin C), Theobroma Cacao (Cocoa) Seed Butter, Tocopheryl Acetate (Vitamin E).

OTHER INFORMATION:

• Protect this product from excessive heat and direct sunlight.